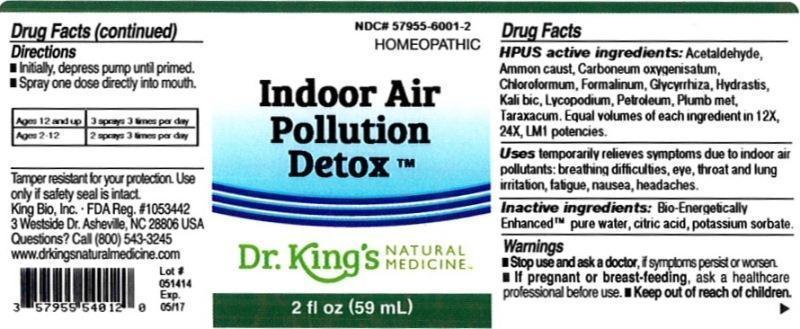 DRUG LABEL: Indoor Air Pollution Detox
NDC: 57955-6001 | Form: LIQUID
Manufacturer: King Bio Inc.
Category: homeopathic | Type: HUMAN OTC DRUG LABEL
Date: 20140528

ACTIVE INGREDIENTS: ACETALDEHYDE 12 [hp_X]/59 mL; AMMONIA 12 [hp_X]/59 mL; CARBON MONOXIDE 12 [hp_X]/59 mL; CHLOROFORM 12 [hp_X]/59 mL; FORMALDEHYDE 12 [hp_X]/59 mL; GLYCYRRHIZA GLABRA 12 [hp_X]/59 mL; GOLDENSEAL 12 [hp_X]/59 mL; POTASSIUM DICHROMATE 12 [hp_X]/59 mL; LYCOPODIUM CLAVATUM SPORE 12 [hp_X]/59 mL; KEROSENE 12 [hp_X]/59 mL; LEAD 12 [hp_X]/59 mL; TARAXACUM OFFICINALE 12 [hp_X]/59 mL
INACTIVE INGREDIENTS: WATER; CITRIC ACID MONOHYDRATE; POTASSIUM SORBATE

Indoor Air Pollution Detox™

ACTIVE INGREDIENT

Drug Facts__________________________________________________________________________________________________________

HPUS activeingredients: Acetaldehyde, Ammonium causticum, Carboneum oxygenisatum, Chloroformum, Formalinum, Glycyrrhiza glabra, Hydrastis canadensis, Kali bichromicum, Lycopodium clavatum, Petroleum, Plumbum metallicum, Taraxacum officinale. Equal volumes of each ingredient in 12X, 24X, LM1 potencies.

INDICATIONS AND USAGE

Uses temporarily relieves symptoms due to indoor air pollutants: breathing difficulties, eye, throat and lung irritation, fatigue, nausea, headaches.

INACTIVE INGREDIENT

Inactive Ingredients: Bio-Energetically Enhanced™ pure water, citric acid and potassium sorbate.

Warnings

- Stop use and ask your doctor if symptoms persist or worsen.
- If pregnant or breast-feeding, ask a healthcare professional before use.

- Keep out of reach of children.

Directions

- Initially, depress pump until primed.
- Spray one dose directly into mouth.
- Ages 12 and up: 3 sprays 3 times per day.
- Ages 2-12: 2 sprays 3 times per day.

OTHER SAFETY INFORMATION

Tamper resistant for your protection. Use only if safety seal is intact.

PURPOSE

Uses temporarily relieves symptoms due to indoor air pollutants:

- breathing difficulties
- eye, throat and lung irritation
- fatigue
- nausea
- headaches